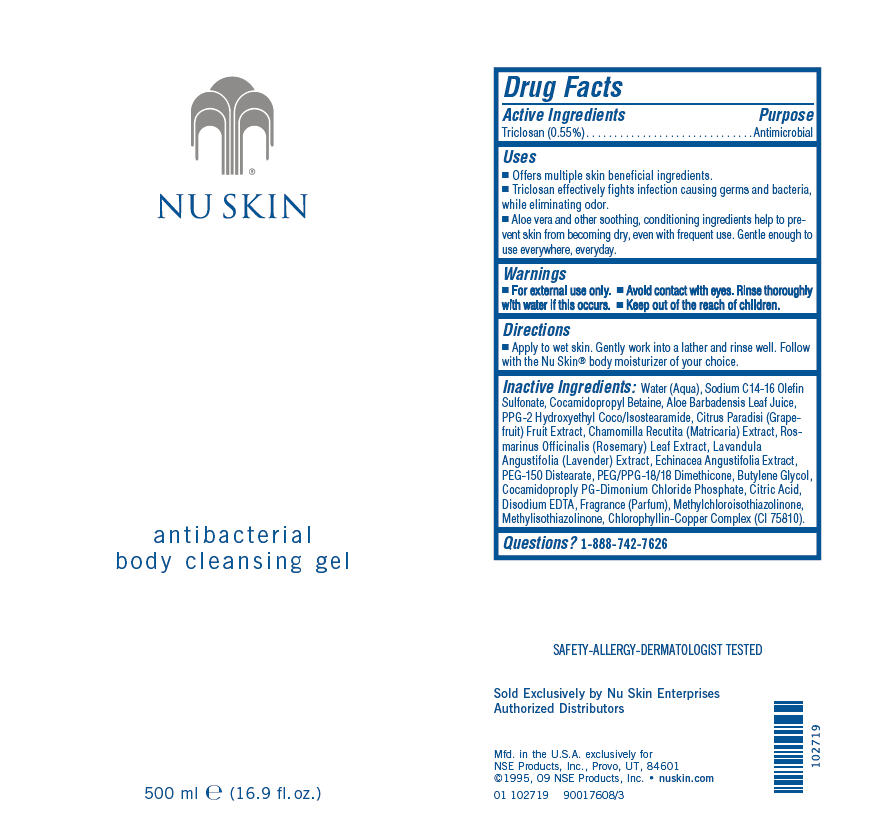 DRUG LABEL: Nu Skin 
NDC: 62839-0271 | Form: GEL
Manufacturer: NSE Products, Inc.
Category: otc | Type: HUMAN OTC DRUG LABEL
Date: 20100813

ACTIVE INGREDIENTS: Triclosan 0.55 mL/100 mL
INACTIVE INGREDIENTS: Water; Sodium C14-16 Olefin Sulfonate; Cocamidopropyl Betaine; Aloe Vera Leaf; Grapefruit; Matricaria Recutita; Rosemary Oil; Lavandula Angustifolia Flowering Top; Echinacea Angustifolia; PEG-150 Distearate; Butylene Glycol; Citric Acid Monohydrate; Edetate Disodium; Methylchloroisothiazolinone; Methylisothiazolinone; Sodium Copper Chlorophyllin

NU SKIN
antibacterial
body cleansing gel

Drug Facts

Active Ingredients

Triclosan (0.55%)

Purpose

Antimicrobial

Uses

- Offers multiple skin beneficial ingredients.
- Triclosan effectively fights infection causing germs and bacteria, while eliminating odor.
- Aloe vera and other soothing, conditioning ingredients help to prevent skin from becoming dry, even with frequent use. Gentle enough to use everywhere, everyday.

Warnings

- For external use only.

WHEN USING

- Avoid contact with eyes. Rinse thoroughly with water if this occurs.

- Keep out of the reach of children.

Directions

- Apply to wet skin. Gently work into a lather and rinse well. Follow with the Nu Skin® body moisturizer of your choice.

Inactive Ingredients

Water (Aqua), Sodium C14-16 Olefin Sulfonate, Cocamidopropyl Betaine, Aloe Barbadensis Leaf Juice, PPG-2 Hydroxyethyl Coco/Isostearamide, Citrus Paradisi (Grapefruit) Fruit Extract, Chamomilla Recutita (Matricaria) Extract, Rosmarinus Officinalis (Rosemary) Leaf Extract, Lavandula Angustifolia (Lavender) Extract, Echinacea Angustifolia Extract, PEG-150 Distearate, PEG/PPG-18/18 Dimethicone, Butylene Glycol, Cocamidoproply PG-Dimonium Chloride Phosphate, Citric Acid, Disodium EDTA, Fragrance (Parfum), Methylchloroisothiazolinone, Methylisothiazolinone, Chlorophyllin-Copper Complex (CI 75810).

Questions?

1-888-742-7626

PRINCIPAL DISPLAY PANEL - 500 ml Bottle Label

NU SKIN

antibacterial
body cleansing gel

500 ml e (16.9 fl. oz.)